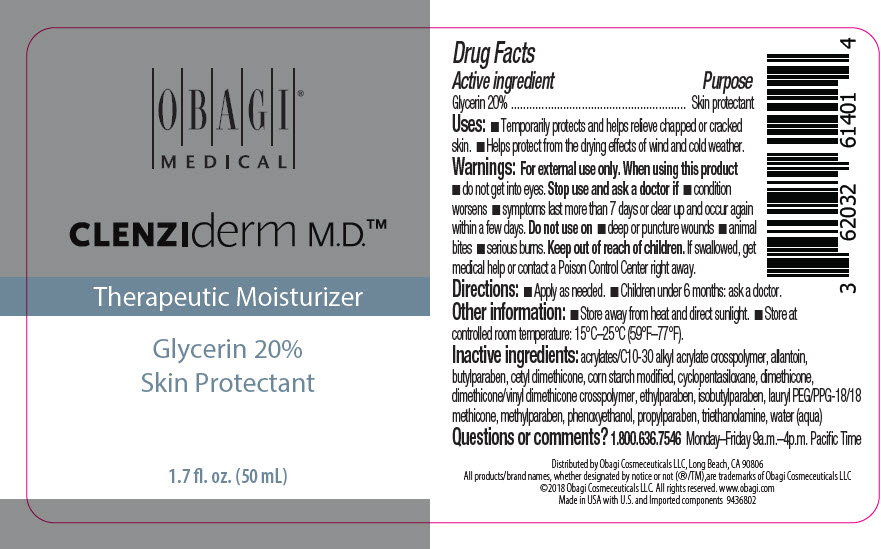 DRUG LABEL: CLENZIDERM THERAPEUTIC MOISTURIZER
NDC: 62032-614 | Form: CREAM
Manufacturer: Obagi Cosmeceuticals LLC
Category: otc | Type: HUMAN OTC DRUG LABEL
Date: 20250101

ACTIVE INGREDIENTS: GLYCERIN 200 mg/1 mL
INACTIVE INGREDIENTS: ALLANTOIN; CARBOMER INTERPOLYMER TYPE A (ALLYL SUCROSE CROSSLINKED); CYCLOMETHICONE 5; LAURYL PEG/PPG-18/18 METHICONE; DIMETHICONE; TROLAMINE; WATER; PHENOXYETHANOL; ETHYLPARABEN; ISOBUTYLPARABEN; BUTYLPARABEN; PROPYLPARABEN; METHYLPARABEN

OBAGI®
Clenziderm M.D.™
Therapeutic
Moisturizer

DRUG FACTS

Active ingredient

Glycerin 20%

Purpose

Skin protectant

Uses

- Temporarily protects and helps relieve chapped or cracked skin.
- Helps protect from the drying effects of wind and cold weather.

Warnings

For external use only

When using this product

- do not get into eyes.

Stop and ask a doctor if

- condition worsens
- symptoms last more than 7 days or clear up and occur again within a few days.

Do not use on

- deep or puncture wounds
- animal bites
- serious burns.

Keep out of reach of children. If swallowed, get medical help or contact a Poison Control Center right away.

Directions

- Apply as needed.
- Children under 6 months: ask a doctor.

Other information

- Store away from heat and direct sunlight.
- Store at controlled room temperature: 15°C–25°C (59°F–77°F)

Inactive ingredients

acrylates/C10-30 alkyl acrylate crosspolymer, allantoin, butylparaben, cetyl dimethicone, corn starch modified, cyclopentasiloxane, dimethicone, dimenthicone/vinyl dimethicone crosspolymer, ethylparaben, isobutylparaben, lauryl PEG/PPG-18/18 methicone, methylparaben, phenoxyethanol, propylparaben, triethanolamine, water

Questions or comments?

1.800.636.7546. Monday-Friday 9a.m.-4p.m. Pacific Time

PRINCIPAL DISPLAY PANEL - 50 mL Bottle Label

OBAGI®
MEDICAL

CLENZIderm M.D.™

Therapeutic Moisturizer
Glycerin 20%
Skin Protectant

1.7 fl. oz. (50 mL)